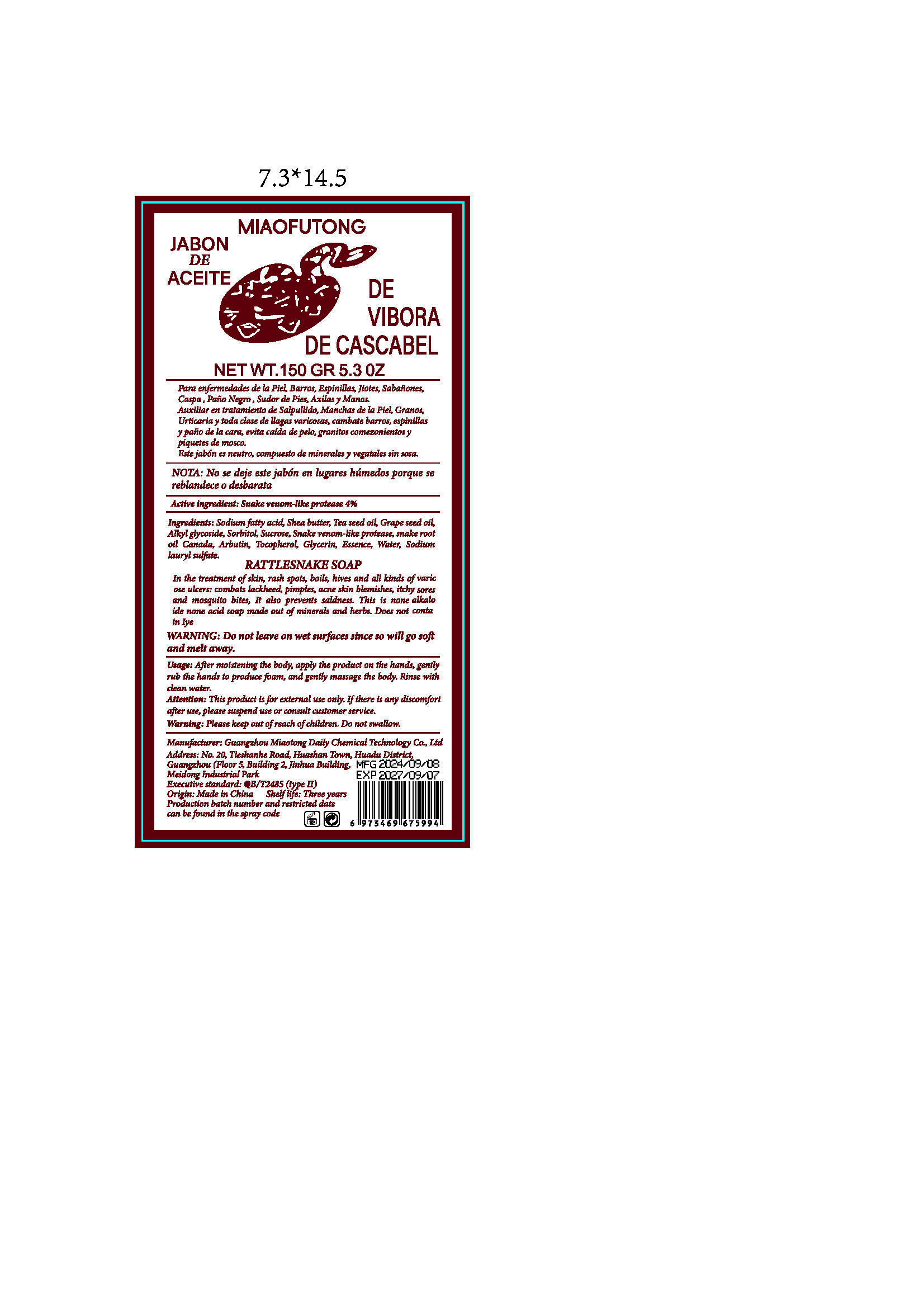 DRUG LABEL: DE  VIBORA  DE CASCABEL
NDC: 84519-004 | Form: SALVE
Manufacturer: Guangzhou Miaotong Daily Chemical Technology Co., Ltd
Category: otc | Type: HUMAN OTC DRUG LABEL
Date: 20240920

ACTIVE INGREDIENTS: DISINTEGRIN AND METALLOPROTEINASE DOMAIN-CONTAINING PROTEIN 17 0.04 g/1 g
INACTIVE INGREDIENTS: GRAPE SEED OIL; TOCOPHEROL; GLYCERIN; SHEA BUTTER; CAMELLIA OIL; COCO GLUCOSIDE; SORBITOL; SUCROSE; SODIUM TALLOWATE, BEEF; ARBUTIN; METHYL BENZOATE; WATER; SODIUM LAURYL SULFATE

DE VIBORA DE CASCABEL

ACTIVE INGREDIENT

SNAKE VENOM-LIKE PROTEASE 4%

PURPOSE

In the treatment ofskin, rash spots, boils, hives and all kinds ofvaricose ulcers: combats lackheed, pimples, acne skin blemishes, itchy soresand mosquito bites, It also prevents saldness. This is none alkaloide none acid soap made out of minerals and herbs. Does not contain Iye

Please keep out ofreach ofchildren. Do not swallow.

INDICATIONS AND USAGE

In the treatment ofskin, rash spots, boils, hives and all kinds ofvaricose ulcers: combats lackheed, pimples, acne skin blemishes, itchy soresand mosquito bites, It also prevents saldness. This is none alkaloide none acid soap made out of minerals and herbs. Does not contain Iye

WARNINGS

Attention: This product is for external use only. Ifthere is any discomfortafter use, please suspend use or consult customer service.
Warning: Please keep out ofreach ofchildren. Do not swallow.
WARNING: Do not leave on wet surfaces since so will go softand melt away.

DOSAGE AND ADMINISTRATION

Usage: After moistening the body, apply the product on the hands, gentlyrub the hands to produce foam, and gently massage the body. Rinse withclean water.

INACTIVE INGREDIENT

Glycerin
Shea butter
Tea seed oil
Grape seed oil
Alkyl glycoside
Sorbitol
Sucrose
Sodium fatty acid
Arbutin
Tocopherol
Essence
Water
Sodium lauryl sulfate